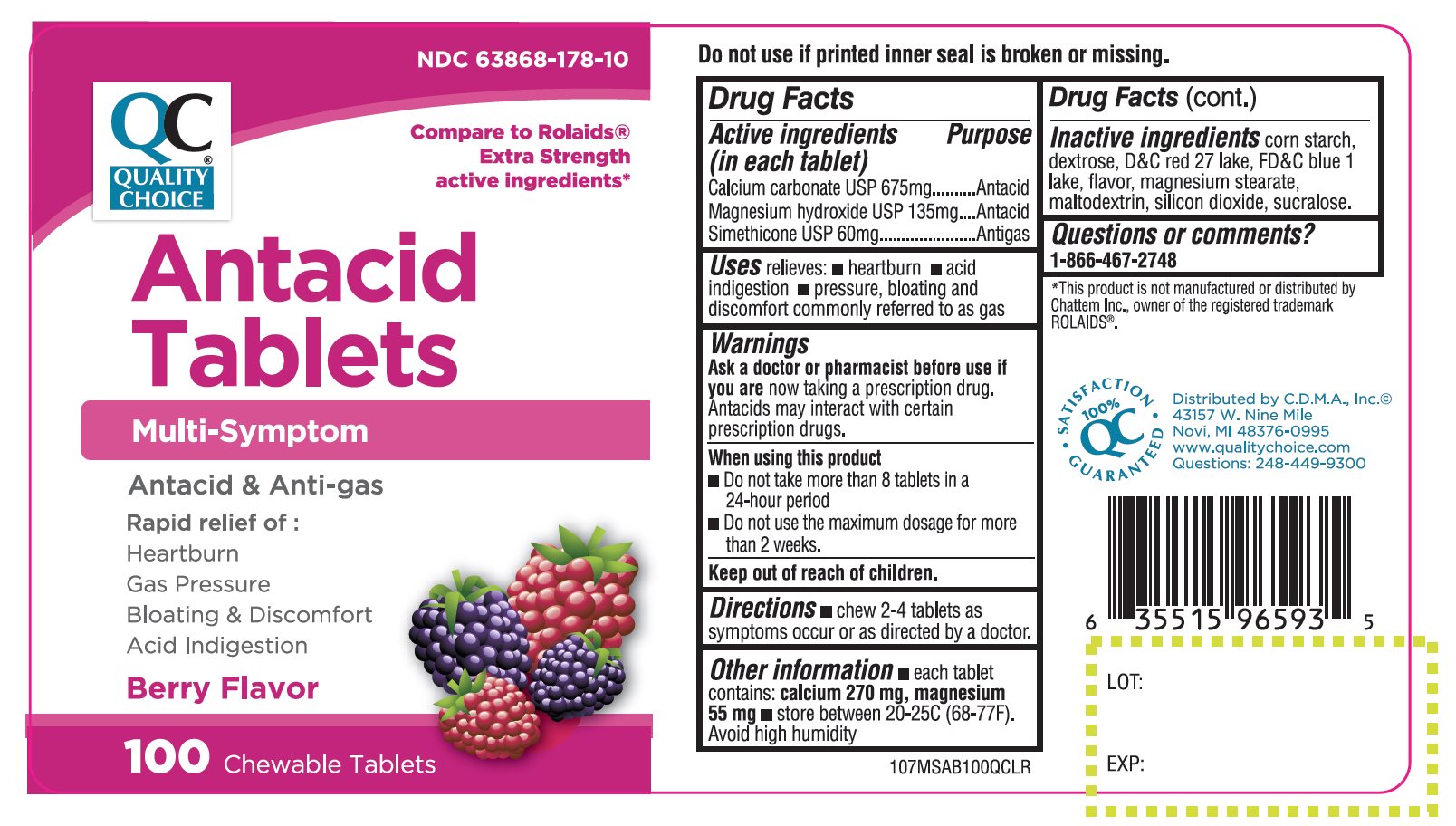 DRUG LABEL: Multi Symptom Antacid
NDC: 63868-178 | Form: TABLET, CHEWABLE
Manufacturer: QUALITY CHOICE (CHAIN DRUG MARKETING ASSOCIATION)
Category: otc | Type: HUMAN OTC DRUG LABEL
Date: 20210121

ACTIVE INGREDIENTS: CALCIUM CARBONATE 675 mg/1 1; MAGNESIUM HYDROXIDE 135 mg/1 1; DIMETHICONE 60 mg/1 1
INACTIVE INGREDIENTS: STARCH, CORN; DEXTROSE, UNSPECIFIED FORM; D&C RED NO. 27; FD&C BLUE NO. 1; MAGNESIUM STEARATE; MALTODEXTRIN; SILICON DIOXIDE; SUCRALOSE

QUALITY CHOICE Multi Symptom 100 Chewable Tablets Berry Flavor

Drug Facts

Active ingredients (in each tablet)

Calcium Carbonate USP 675 mg
Magnesium hydroxide USP 135 mg

Simethicone USP 60mg

Purpose

Antacid

Antacid

Antigas

Uses

relieves:

- heartburn
- acid indigestion
- pressure, bloating and discomfort commonly referred to as gas

Warnings

Ask a doctor or pharmacist before use if you are

now taking a prescription drug. Antacids may interact with certain prescription drugs.

When using this product

- Do not take more than 8 tablets in a 24-hour period
- Do not use the maximum dosage for more than 2 weeks

Directions

- chew 2-4 tablets completely as symptoms occur or as directed by a doctor.

Other information

- each tablet contains: calcium 270 mg, magnesium 55 mg
- store between 20-25C (68-77F).

Avoid high humidity

Inactive ingredients

corn starch, dextrose, D&C Red No. 27 lake, FD&C Blue No. 1 lake, flavor, magnesium stearate, maltodextrin, silicon dioxide, sucralose.

Questions?

1-866-467-2748

PRINCIPAL DISPLAY PANEL

NDC# 63868-178-10

Compare To Rolaids® Extra Strength active ingredients*

Antacid Tablets

Multi-Symptom

Antacid & Anti-gas

Rapid relief of:

Heartburn

Gas Pressure

Bloating & Discomfort

Acid Indigestion

Berry Flavor

100 CHEWABLE TABLETS

100% QC SATISFACTION GURANTEED

Distributed by C.D.M.A., Inc.©

41357 W. Nine Mile

Novi, MI 48376-0995

www.qualitychoice.com

Questions: 248-449-9300

*This product is not manufactured or distributed by Chattem Inc., owner of the registered trademark ROLAIDS®

TAMPER EVIDENT: DO NOT USE IF PRINTED INNER SEAL IS BROKEN OR MISSING.